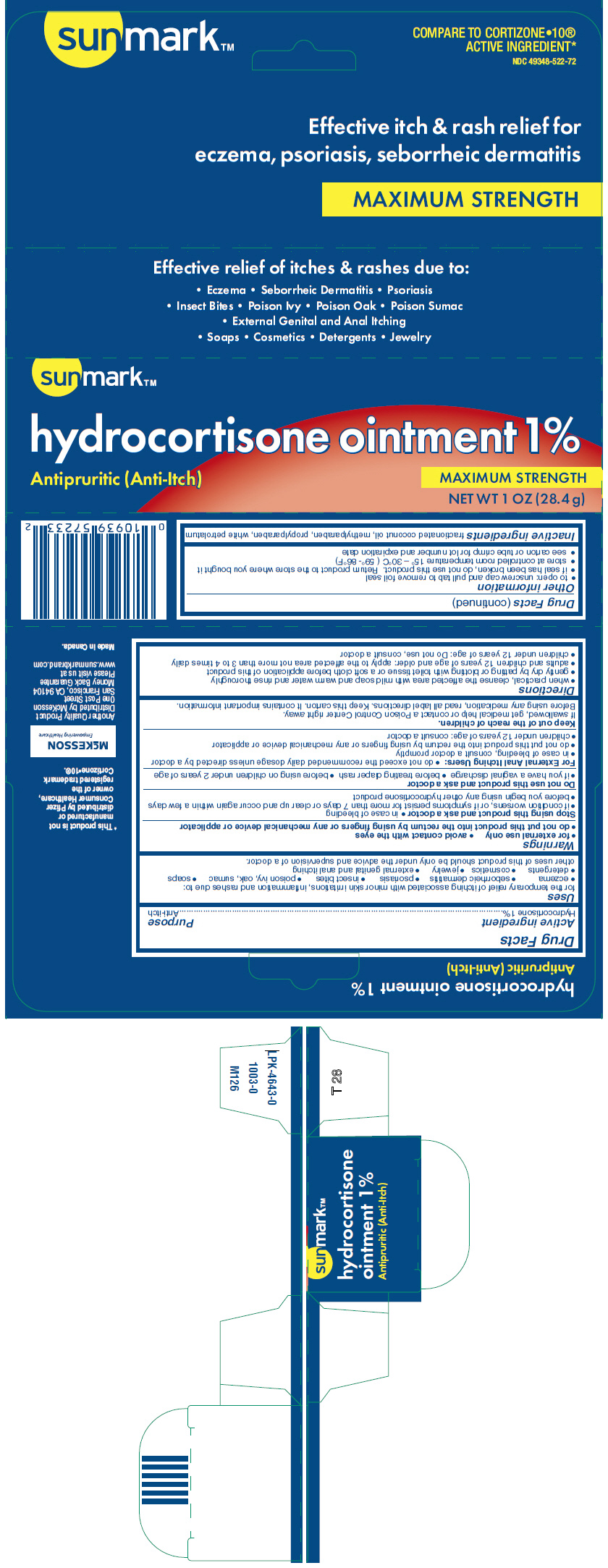 DRUG LABEL: sunmark
NDC: 49348-522 | Form: OINTMENT
Manufacturer: Strategic Sourcing Services LLC
Category: otc | Type: HUMAN OTC DRUG LABEL
Date: 20250707

ACTIVE INGREDIENTS: HYDROCORTISONE 1 g/100 g
INACTIVE INGREDIENTS: MEDIUM-CHAIN TRIGLYCERIDES; METHYLPARABEN; PROPYLPARABEN; PETROLATUM

sunmark™
Hydrocortisone

Drug Facts

Active ingredient

Hydrocortisone 1%

Purpose

Anti-itch

Uses

for the temporary relief of itching associated with minor skin irritations, inflammation and rashes due to:

- eczema
- seborrheic dermatitis
- psoriasis
- insect bites
- poison ivy, oak, sumac
- soaps
- detergents
- cosmetics
- jewelry
- external genital and anal itching

other uses of this product should be only under the advice and supervision of a doctor.

Warnings

- for external use only
- avoid contact with the eyes
- do not put this product into the rectum by using fingers or any mechanical device or applicator

Stop using this product and ask a doctor

- in case of bleeding
- if condition worsens, or if symptoms persist for more than 7 days or clear up and occur again within a few days
- before you begin using any other hydrocortisone product

Do not use this product and ask a doctor

- if you have a vaginal discharge
- before treating diaper rash
- before using on children under 2 years of age

For External Anal Itching Users

- do not exceed the recommended daily dosage unless directed by a doctor
- in case of bleeding, consult a doctor promptly
- do not put this product into the rectum by using fingers or any mechanical device or applicator
- children under 12 years of age: consult a doctor

Keep out of the reach of children.

If swallowed, get medical help or contact a Poison Control Center right away.

Before using any medication, read all label directions. Keep this carton. It contains important information.

Directions

- when practical, cleanse the affected area with mild soap and warm water and rinse thoroughly
- gently dry by patting or blotting with toilet tissue or a soft cloth before application of this product
- adults and children 12 years of age and older: apply to the affected area not more than 3 to 4 times daily
- children under 12 years of age: Do not use, consult a doctor

Other information

- to open: unscrew cap and pull tab to remove foil seal
- if seal has been broken, do not use this product. Return product to the store where you bought it
- store at controlled room temperature 15° – 30°C (59°- 86°F)
- see carton or tube crimp for lot number and expiration date

Inactive ingredients

fractionated coconut oil, methylparaben, propylparaben, white petrolatum

Distributed by McKesson
One Post Street
San Francisco, CA 94104

PRINCIPAL DISPLAY PANEL - 28.4 g Tube Carton

sunmark™

hydrocortisone ointment 1%

Antipruritic (Anti-Itch)

MAXIMUM STRENGTH

NET WT 1 OZ (28.4 g)